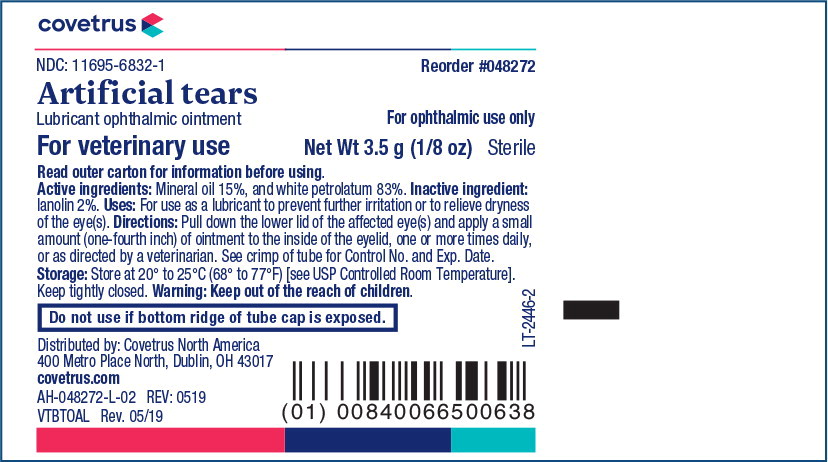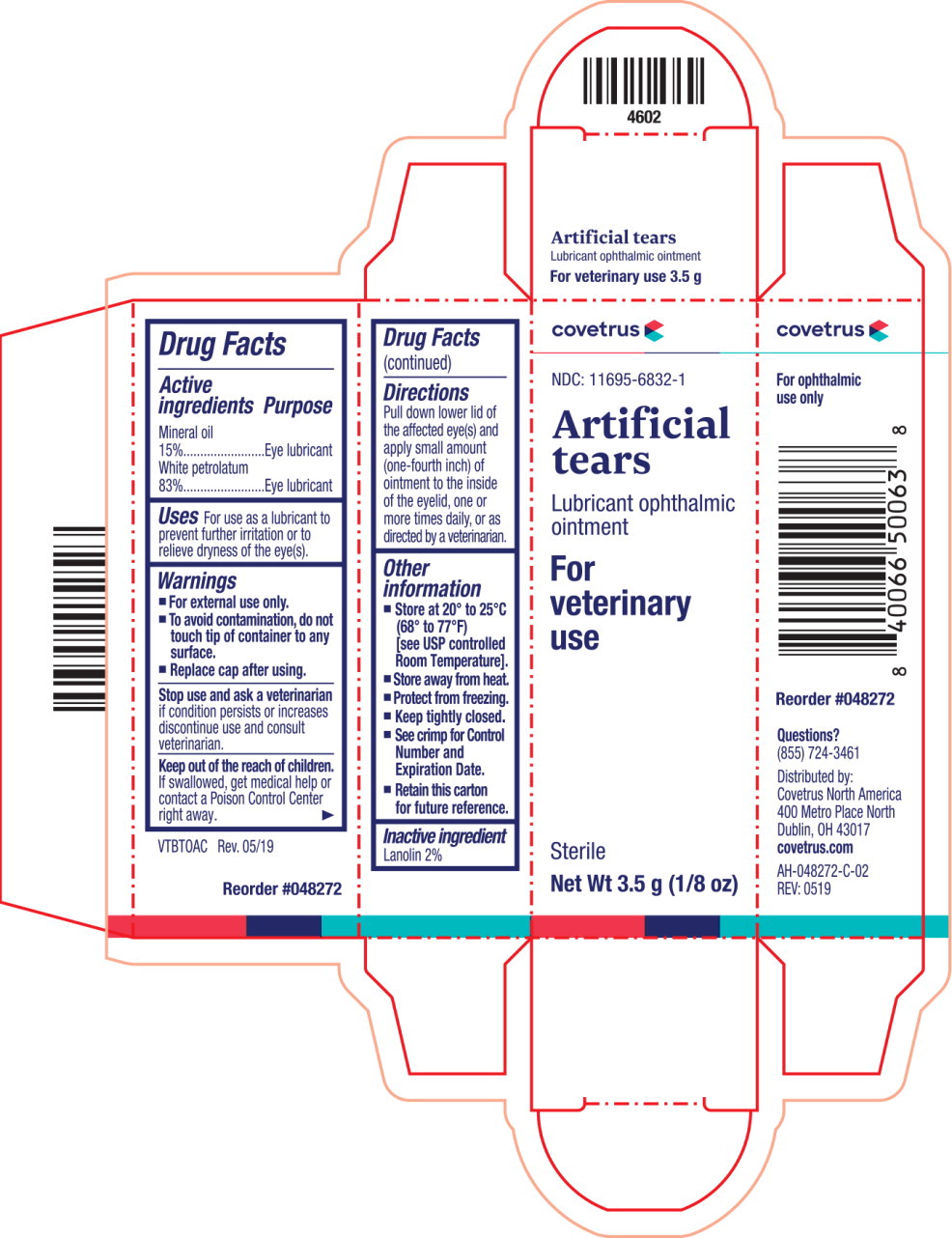 DRUG LABEL: Artificial tears
NDC: 11695-6832 | Form: OINTMENT
Manufacturer: Butler Animal Health Supply, LLC dba Covetrus North America
Category: animal | Type: OTC ANIMAL DRUG LABEL
Date: 20220208

ACTIVE INGREDIENTS: Mineral Oil 150 mg/1 g; Petrolatum 830 mg/1 g
INACTIVE INGREDIENTS: Lanolin

Drug Facts

Active ingredients

Mineral oil 15%

White petrolatum 83%

Purpose

Eye lubricant

Eye lubricant

Uses

For use as a lubricant to prevent further irritation or to relieve dryness of the eye(s).

Warnings

- For external use only.
- To avoid contamination, do not touch tip of container to any surface.
- Replace cap after using.

Stop use and ask a veterinarian if condition persists or increases discontinue use and consult veterinarian.

Keep out of the reach of children.

If swallowed, get medical help or contact a Poison Control Center right away.

Directions

Pull down lower lid of the affected eye(s) and apply small amount (one-fourth inch) of ointment to the inside of the eyelid, one or more times daily, or as directed by a veterinarian.

Other information

- Store at 20° to 25°C (68° to 77°F) [see USP controlled Room Temperature].
- Store away from heat.
- Protect from freezing.
- Keep tightly closed.
- See crimp for Control Number and Expiration Date.
- Retain this carton for future reference.

Inactive ingredient

Lanolin 2%

Principal Display Panel Text for Container Label:

covetrus logo

NDC: 11695-6832-1 Reorder #048272

Artificial tears

Lubricant ophthalmic ointment For ophthalmic use only

For veterinary use Net Wt 3.5 g (1/8 oz) Sterile

Principal Display Panel Text for Carton Label:

covetrus logo

NDC: 11695-6832-1

Artificial

tears

Lubricant ophthalmic

ointment

For

veterinary

use

Sterile

Net Wt 3.5 g (1/8 oz)